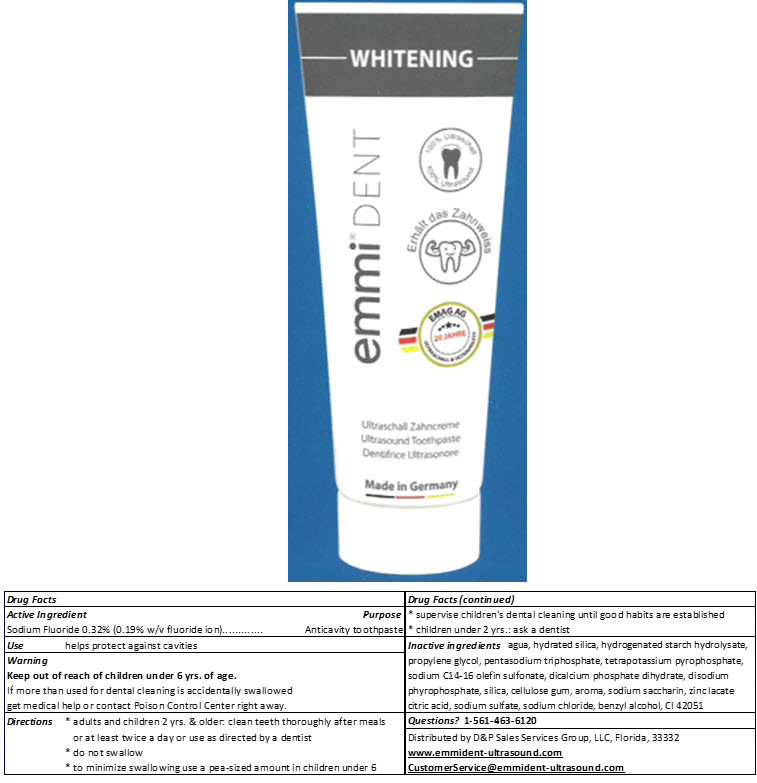 DRUG LABEL: Emmi-dent Whitening
NDC: 63956-003 | Form: PASTE, DENTIFRICE
Manufacturer: EMAG AG
Category: otc | Type: HUMAN OTC DRUG LABEL
Date: 20241203

ACTIVE INGREDIENTS: Sodium Fluoride 320 mg/75 mL
INACTIVE INGREDIENTS: Water; Hydrated Silica; Hydrogenated Starch Hydrolysate; Propylene Glycol; Sodium Tripolyphosphate Anhydrous; POTASSIUM PYROPHOSPHATE; Sodium C14-16 Olefin Sulfonate; DIBASIC CALCIUM PHOSPHATE DIHYDRATE; SODIUM ACID PYROPHOSPHATE; SILICON DIOXIDE; Cellulose Gum; Saccharin Sodium; Zinc Lactate; CITRIC ACID MONOHYDRATE; Sodium Sulfate; Sodium Chloride; Benzyl Alcohol; PATENT BLUE V

Emmi®-dent Whitening

Drug Facts

Active Ingredient

Sodium Fluoride 0.32% (0.19% w/v fluoride ion)

Purpose

Anticavity toothpaste

Use

helps protect against cavities

Warning

Keep out of reach of children under 6 yrs. of age.

If more than used for dental cleaning is accidentally swallowed, get medical help or contact a Poison Control Center right away.

Directions

- adults and children 2 yrs. & older: clean teeth thoroughly after meals or at least twice a day or use as directed by a dentist
- do not swallow
- to minimize swallowing use a pea-sized amount in children unter 6
- supervise children's dental cleaning until good habits are established
- children under 2 yrs.: ask a dentist

Inactive ingredients

Agua, hydrated silica, hydrogenated starch hydrolysate, propylene glycol, penta sodium triphosphate, tetra potassium pyrophosphate, sodium C14-16 olefin sulfonate, dicalcium phosphate dihydrate, disodium pyrophosphate, silica, cellulose gum, aroma, sodium saccharin, zinc lactate citric acid, sodium sulfate, sodium chloride, benzyl alcohol, CI 42051

Questions?

1-833-682-8902

Distributed by Ultra Oral Care Inc.,
Spring, Texas, 77386

PRINCIPAL DISPLAY PANEL - 75 mL Tube Carton

emmi® DENT

WHITENING

emmi® DENT

100% Ultrasound

Ultrasound Toothpaste

Made in Germany

Ideal
100% Ultraschall®
Made by EMAG Germany